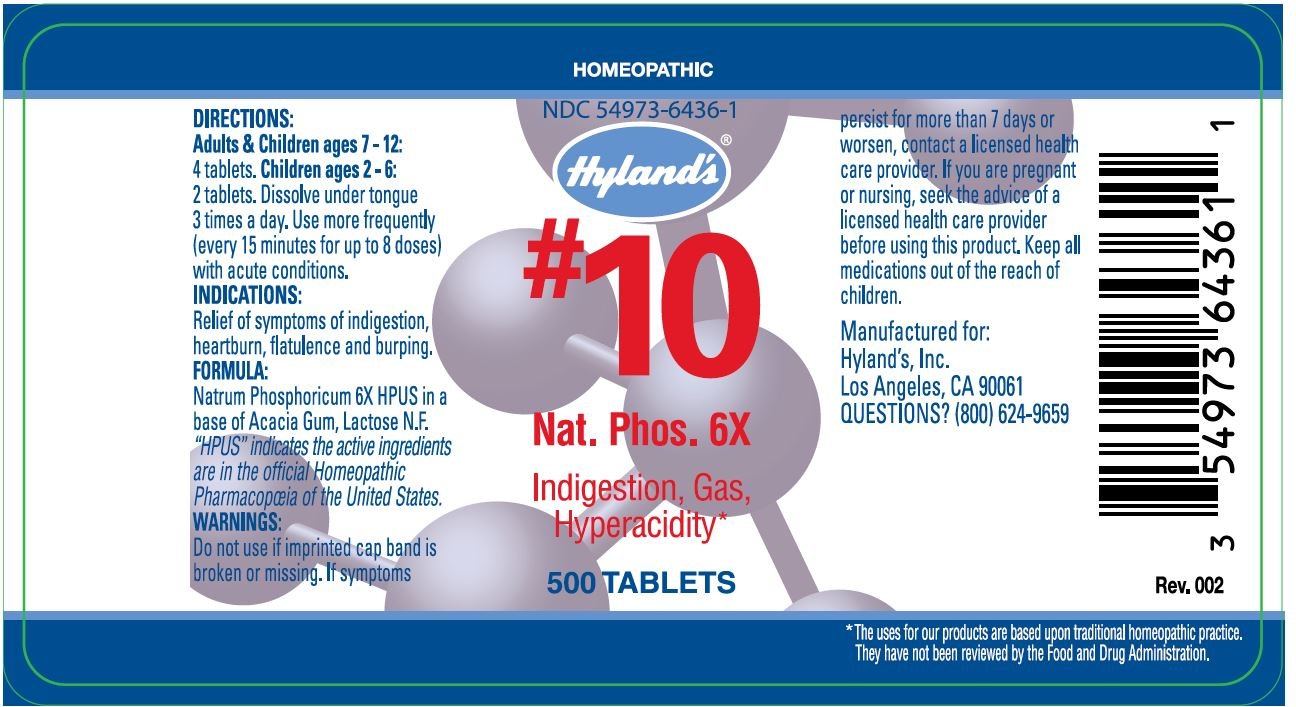 DRUG LABEL: NAT. PHOS.
NDC: 54973-6436 | Form: TABLET
Manufacturer: Hyland's Inc.
Category: homeopathic | Type: HUMAN OTC DRUG LABEL
Date: 20221219

ACTIVE INGREDIENTS: SODIUM PHOSPHATE, DIBASIC, ANHYDROUS 6 [hp_X]/1 1
INACTIVE INGREDIENTS: ACACIA; LACTOSE

#10 Natrum Phosphoricum 6X

DIRECTIONS

Adults & Children ages 7 - 12: 4 tablets. Children ages 2 - 6: 2 tablets. Dissolve under tongue 3 times a day. Use more frequently (every 15 minutes for up to 8 doses) with acute conditions.

INDICATIONS

PURPOSE

Relief of symptoms of indigestion, heartburn, flatulence and burping.

FORMULA

Natrum Phosphoricum 6X HPUS

INACTIVE INGREDIENT

In a base of Acacia Gum, Lactose N.F.

“HPUS” indicates that the active ingredients are in the official Homeopathic Pharmacopœia of the United States.

Warnings

Do not use if imprinted cap band is broken or missing.

ASK DOCTOR/PHARMACIST

If symptoms persist for more than 7 days or worsen, contact a licensed health care provider.

PREGNANCY OR BREAST FEEDING

If you are pregnant or nursing, seek the advice of a licensed health care provider before using this product.

KEEP OUT OF REACH OF CHILDREN

Keep all medications out of the reach of children.

QUESTIONS?

(800) 624-9659

PRINCIPAL DISPLAY PANEL - 500 Tablet Bottle Label

HOMEOPATHIC

NDC 54973-6436-01

Hyland's®

#10
Nat. Phos. 6X

Indigestion, Gas,
Hyperacidity*

500 TABLETS